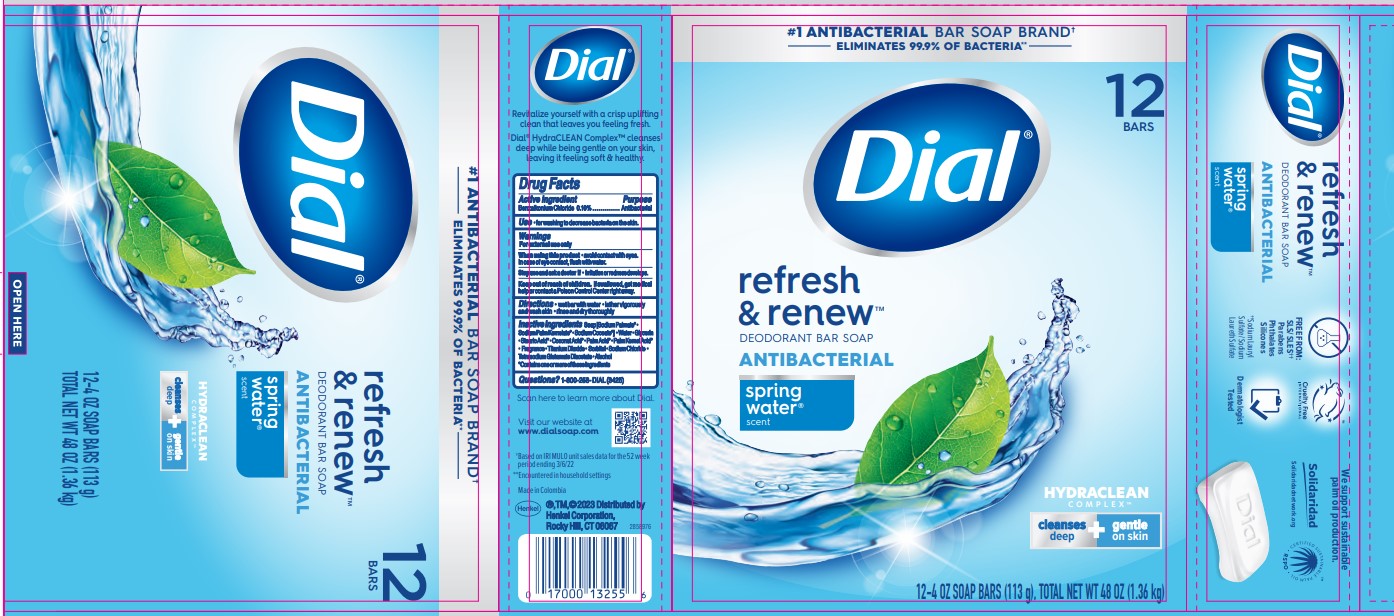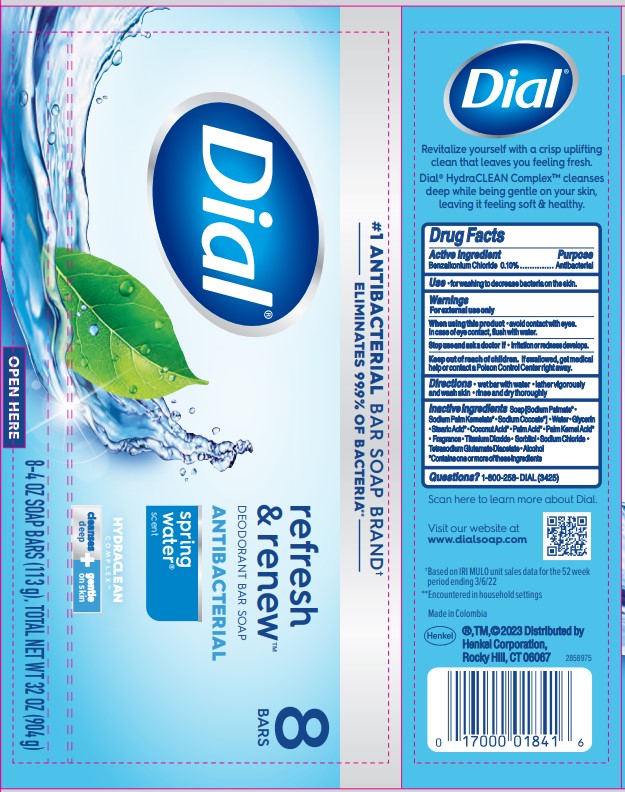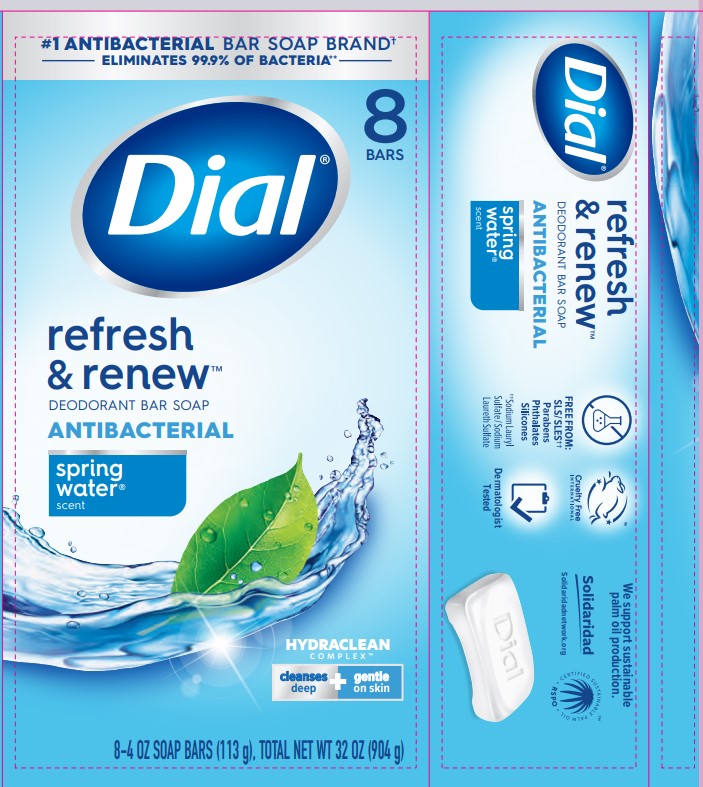 DRUG LABEL: Dial Complete Antibacterial Bar
NDC: 54340-270 | Form: SOAP
Manufacturer: Henkel Corporation
Category: otc | Type: HUMAN OTC DRUG LABEL
Date: 20251113

ACTIVE INGREDIENTS: BENZALKONIUM CHLORIDE 0.1 g/100 g
INACTIVE INGREDIENTS: WATER 13.95 g/100 g; SODIUM CHLORIDE 0.39 g/100 g; GLYCERIN 8.05 g/100 g; SODIUM PALMATE 61.81 g/100 g; STEARIC ACID 2.434 g/100 g; ALCOHOL 0.01 g/100 g; SODIUM PALM KERNELATE 11 g/100 g; TITANIUM DIOXIDE 0.8 g/100 g; SORBITOL 0.5525 g/100 g; TETRASODIUM GLUTAMATE DIACETATE 0.058 g/100 g

Dial Complete Antibacterial Soap - Spring Water,
Dial Complete Spring Water Antibacterial Deodarant Soap,
Dial Spring Water Antibacterial Soap
Dial Refresh & Renew Deodorant Bar Soap Antibacterial Spring Water Scent

Drug Facts

Active ingredient

Benzalkonium Chloride 0.10%

Purpose

Antibacterial

Use

For washing to decrease bacteria on the skin.

Warnings

For external use only.

When using this product avoid contact with the eyes. In case of eye contact, flush with water.

Stop use and ask a doctor if irritation and redness develops.

Keep out of reach of children. If swallowed, get medical help or contact a Poison Control Center right away.

Directions

Wet bar with water. Lather vigorously and wash skin. Rinse and dry thoroughly.

INACTIVE INGREDIENT

Soap[Sodium Palmate* · Sodium Palm Kernelate* · Sodium Cocoate*] · Water · Glycerin · Stearic Acid* · Coconut Acid* · Palm Acid* · Palm Kernel Acid* · Fragrance · Titanium Dioxide · Sorbitol · Sodium Chloride · Tetrasodium Glutamate Diacetate · Alcohol
*Contains one or more of these ingredients

Questions? 1-800-258-DIAL (3425)

Visit our website at www.dialsoap.com

Henkel®, TM, ©2023

Distributed by

Henkel Corporation,

Rocky Hill, CT 06067

Made in Columbia